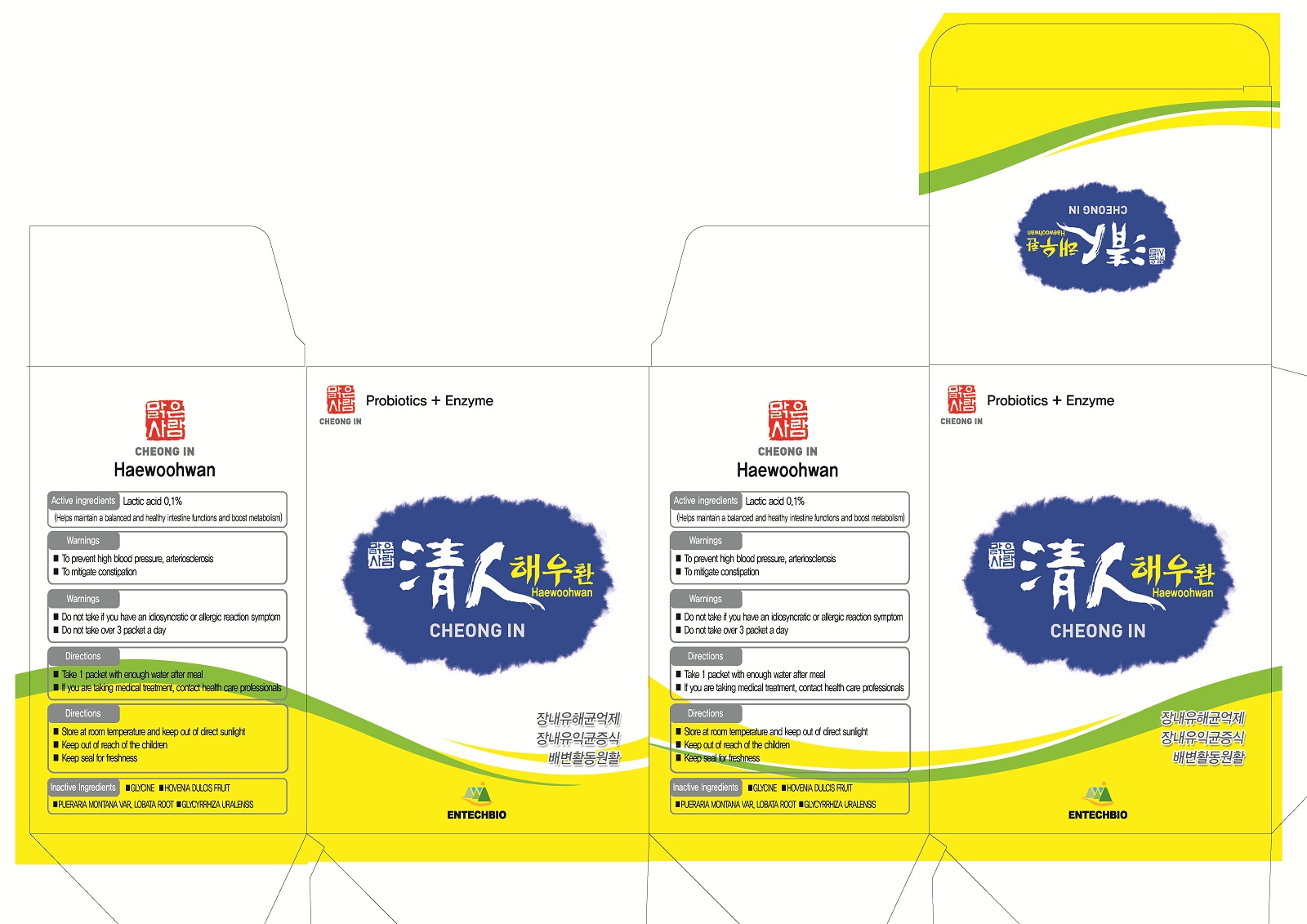 DRUG LABEL: Cheongin Haewoohwan
NDC: 75863-3001 | Form: PELLET
Manufacturer: Entechbio Co., Ltd
Category: otc | Type: HUMAN OTC DRUG LABEL
Date: 20110218

ACTIVE INGREDIENTS: LACTIC ACID 0.001 g/1 g
INACTIVE INGREDIENTS: GLYCINE; HOVENIA DULCIS FRUIT; PUERARIA MONTANA VAR. LOBATA ROOT; GLYCYRRHIZA URALENSIS

Drug Facts

active ingredient: lactic acid (lactobacillus casei, lactobacillus bifidus)

inactive ingredient: GLYCINE, HOVENIA DULCIS FRUIT, PUERARIA MONTANA VAR. LOBATA ROOT, GLYCYRRHIZA URALENSIS

PURPOSE

to prevent high blood pressure, arteriosclerosis
to mitigate constipation

keep out of reach of the children

INDICATIONS AND USAGE

take 1 packet with enough water after meal

WARNINGS

do not take if you have an idiosyncratic of allergic reaction symptom
do not take over 3 packet a day

DOSAGE AND ADMINISTRATION

take continuously even if you feel improvement of physical constitution